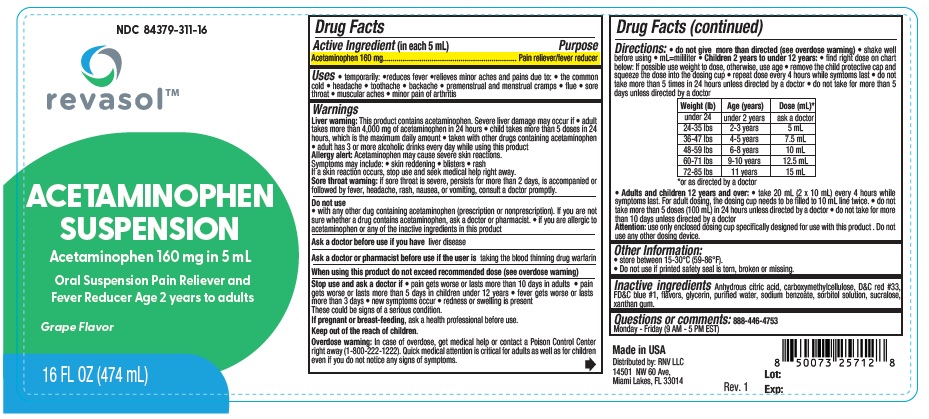 DRUG LABEL: Revasol Acetaminophen Suspension
NDC: 84379-311 | Form: LIQUID
Manufacturer: Rnv LLC
Category: otc | Type: HUMAN OTC DRUG LABEL
Date: 20260213

ACTIVE INGREDIENTS: ACETAMINOPHEN 160 mg/5 mL
INACTIVE INGREDIENTS: SORBITOL SOLUTION; CARBOXYMETHYLCELLULOSE SODIUM; SUCRALOSE; SODIUM BENZOATE; XANTHAN GUM; GLYCERIN; D&C RED NO. 33; WATER; CITRIC ACID; FD&C BLUE NO. 1

Revasol Acetaminophen Suspension NDC 84379-311-16

ACTIVE INGREDIENT

Acetaminophen 160 mg

PURPOSE

Pain reliever/fever reducer

Uses

• temporarily: •reduces fever •relieves minor aches and pains due to: • the common
cold • headache • toothache • backache • premenstrual and menstrual cramps • flue • sore
throat • muscular aches • minor pain of arthritis

Warnings

Liver warning: This product contains acetaminophen. Severe liver damage may occur if • adult
takes more than 4,000 mg of acetaminophen in 24 hours • child takes more than 5 doses in 24
hours, which is the maximum daily amount • taken with other drugs containing acetaminophen
• adult has 3 or more alcoholic drinks every day while using this product
Allergy alert: Acetaminophen may cause severe skin reactions.
Symptoms may include: • skin reddening • blisters • rash
If a skin reaction occurs, stop use and seek medical help right away.
Sore throat warning: if sore throat is severe, persists for more than 2 days, is accompanied or
followed by fever, headache, rash, nausea, or vomiting, consult a doctor promptly.

Do not use
• with any other dug containing acetaminophen (prescription or nonprescription). If you are not
sure whether a drug contains acetaminophen, ask a doctor or pharmacist. • if you are allergic to
acetaminophen or any of the inactive ingredients in this product

Ask a doctor before use if you have liver disease

Ask a doctor or pharmacist before use if the user is taking the blood thinning drug warfarin

When using this product do not exceed recommended dose (see overdose warning)

Stop use and ask a doctor if • pain gets worse or lasts more than 10 days in adults • pain
gets worse or lasts more than 5 days in children under 12 years • fever gets worse or lasts
more than 3 days • new symptoms occur • redness or swelling is present
These could be signs of a serious condition.

PREGNANCY OR BREAST FEEDING

If pregnant or breast-feeding, ask a health professional before use.

Keep out of the reach of children.

OVERDOSAGE

Overdose warning: In case of overdose, get medical help or contact a Poison Control Center
right away (1-800-222-1222). Quick medical attention is critical for adults as well as for children
even if you do not notice any signs of symptoms.

Directions:

• do not give more than directed (see overdose warning) • shake well
before using • mL=mililiter • Children 2 years to under 12 years: • find right dose on chart
below: If possible use weight to dose, otherwise, use age • remove the child protective cap and
squeeze the dose into the dosing cup • repeat dose every 4 hours while symtoms last • do not
take more than 5 times in 24 hours unless directed by a doctor • do not take for more than 5
days unless directed by a doctor

Weight (lb) | Age (years) | Dose (mL)*
under 24 | under 2 years | ask a doctor
24-35 lbs | 2-3 years | 5 mL
36-47 lbs | 4-5 years | 7.5 mL
48-59 lbs | 6-8 years | 10 mL
60-71 lbs | 9-10 years | 12.5 mL
72-85 lbs | 11 years | 15 mL

*or as directed by a doctor

• Adults and children 12 years and over: • take 20 mL (2 x 10 mL) every 4 hours while

symptoms last. For adult dosing, the dosing cup needs to be filled to 10 mL line twice. • do not
take more than 5 doses (100 mL) in 24 hours unless directed by a doctor • do not take for more
than 10 days unless directed by a doctor
Attention: use only enclosed dosing cup specifically designed for use with this product . Do not
use any other dosing device.

Other Information:
• store between 15-30°C (59-86°F).
• Do not use if printed safety seal is torn, broken or missing.

INACTIVE INGREDIENT

Inactive ingredients Anhydrous citric acid, carboxymethylcellulose, D&C red #33,
FD&C blue #1, flavors, glycerin, purified water, sodium benzoate, sorbitol solution, sucralose,
xanthan gum.

Questions or comments: 888-446-4753
Monday - Friday (9 AM - 5 PM EST)